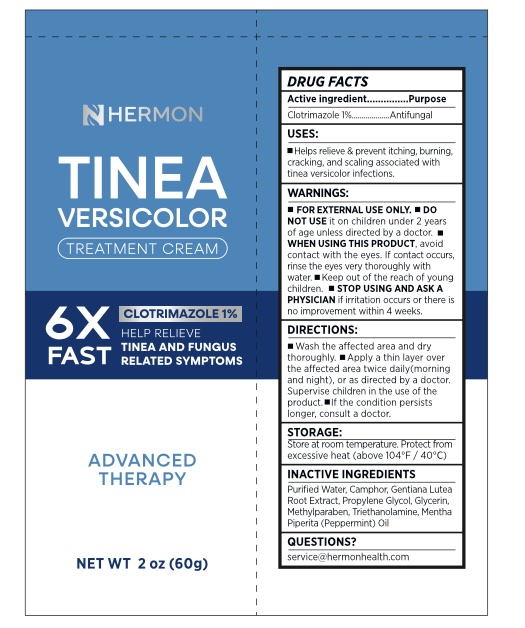 DRUG LABEL: Tinea Versicolor Treatment Cream
NDC: 85398-002 | Form: CREAM
Manufacturer: Beautivity LLC
Category: otc | Type: HUMAN OTC DRUG LABEL
Date: 20260302

ACTIVE INGREDIENTS: CLOTRIMAZOLE 10 mg/1 g
INACTIVE INGREDIENTS: WATER; PEPPERMINT OIL; CAMPHOR (SYNTHETIC); TRIETHANOLAMINE; GLYCERIN; PROPYLENE GLYCOL; METHYLPARABEN; GENTIANA LUTEA ROOT

Update-85398-002-01

ACTIVE INGREDIENT

Clotrimazole 1%

PURPOSE

Antifungal

INDICATIONS AND USAGE

Helps relieve & prevent itching, burning, cracking, and scaling associated with tinea nersicolor infections.

WARNINGS

For External Use Only

DO NOT USE

it on children under 2 years of age unless directed by a doctor.

WHEN USING

avoid contact with eyes, if contact occurs, rinse the eyes very thoroughly with water.

STOP USE

Stop Using and Ask a Physician if irritation occurs or there is no improvement within 4 weeks.

keep out of the reach of young children.

DOSAGE AND ADMINISTRATION

- Wash the affected area and dry thoroughly.
- Apply a thin layer over the affected area twice daily (morning and night), or as directed by a doctor, supervise children in the use of the product.
- If the condition persists longer, consult a doctor.

STORAGE AND HANDLING

Store at room temperature. Protect from excessive heat (above 104ºF/40ºC)

INACTIVE INGREDIENT

Purified Water, Camphor, Gentiana Lutea Root, Propylene Glycol, Glycerin, Methylparaben, Triethanolamine, Peppermint Oil

QUESTIONS

service@hermonhealth.com